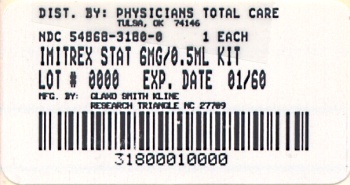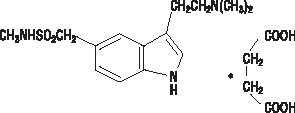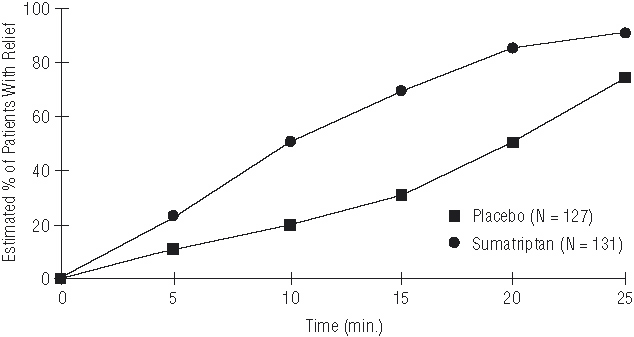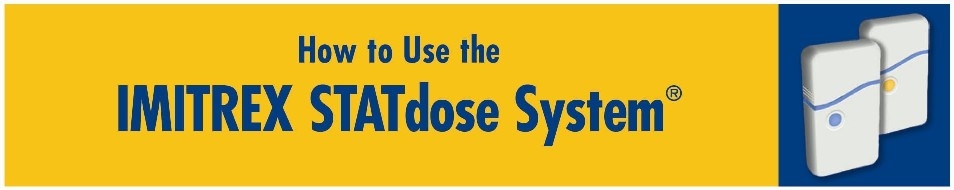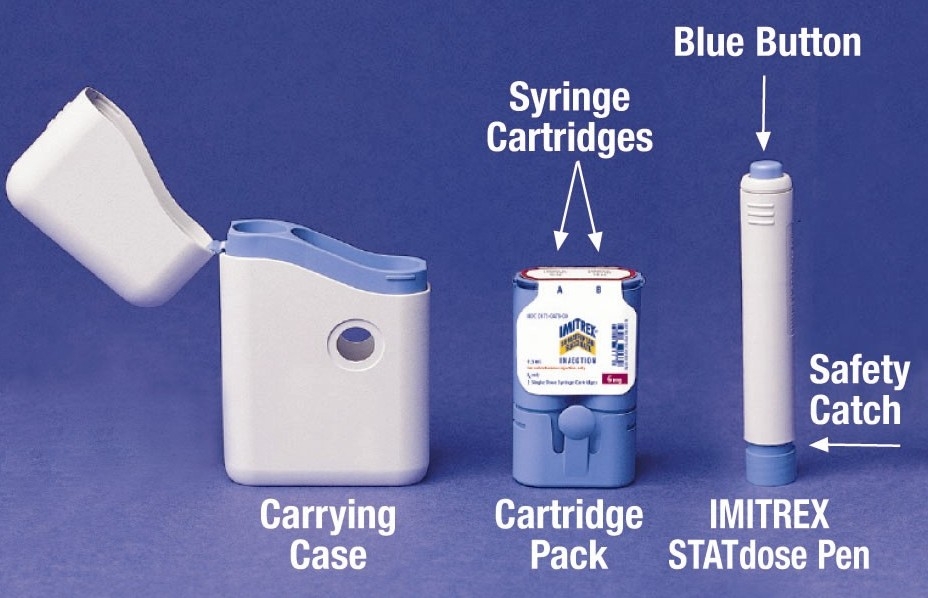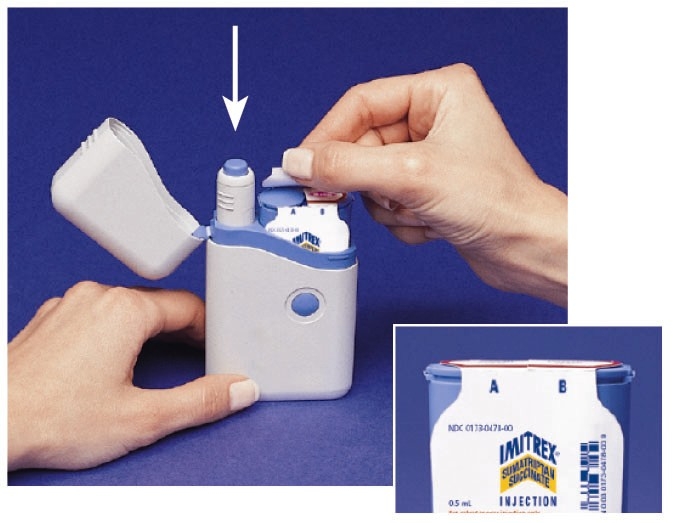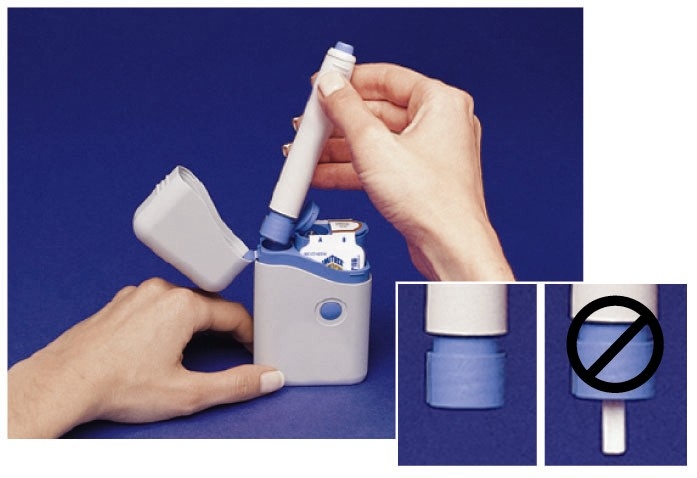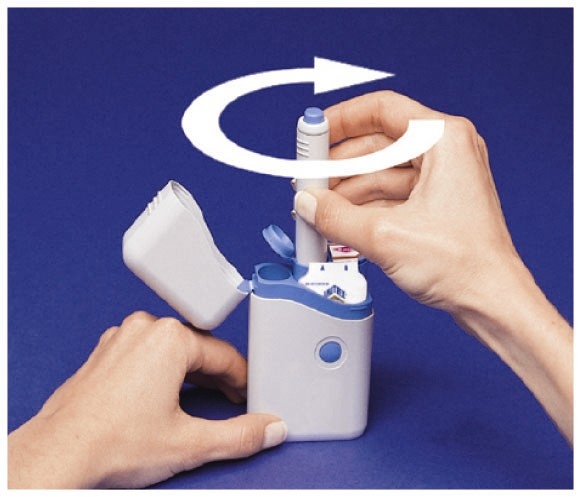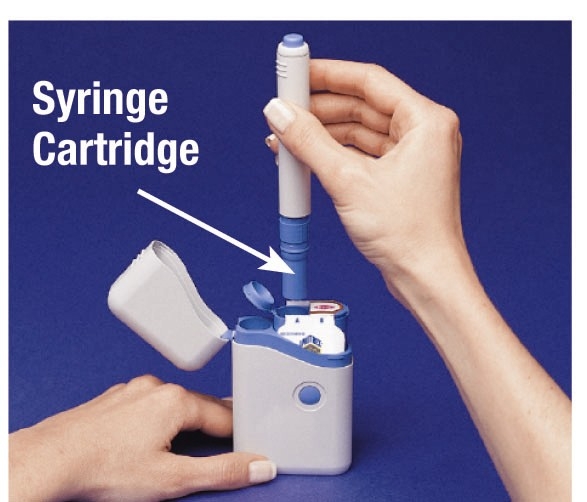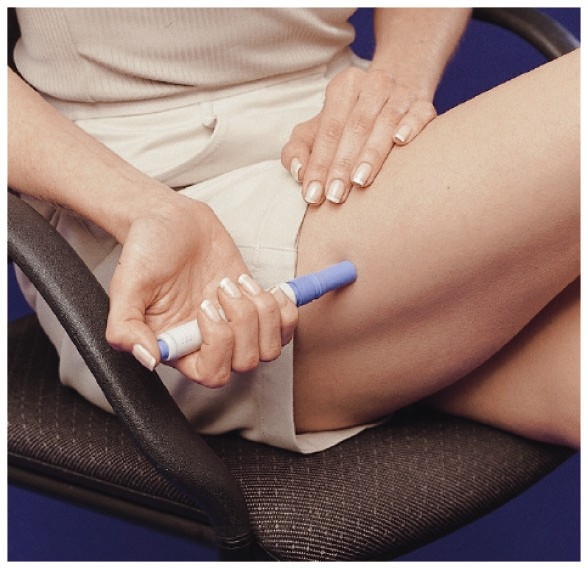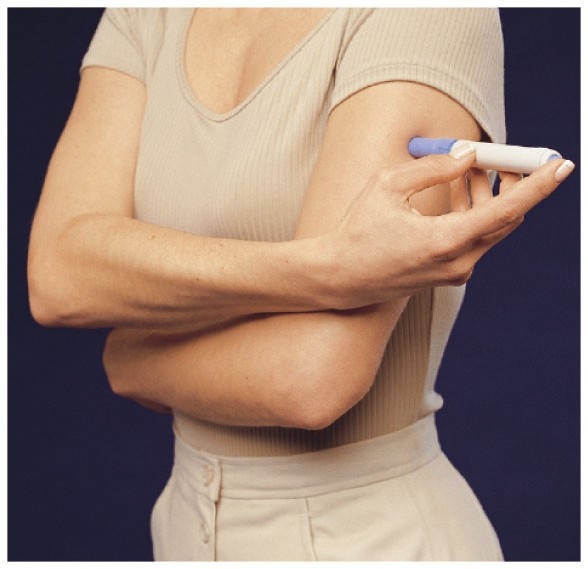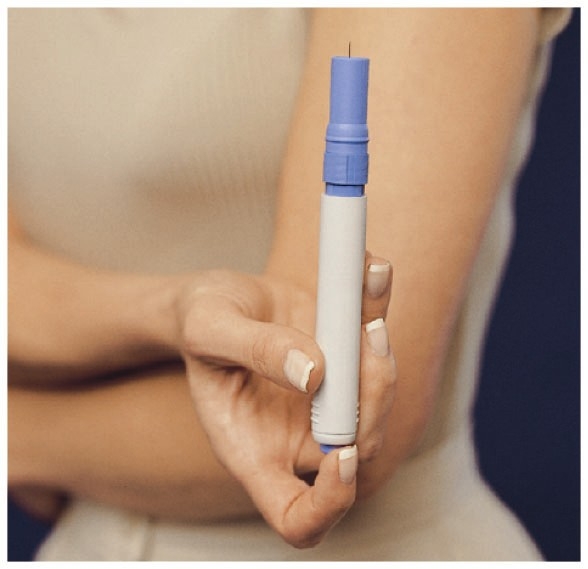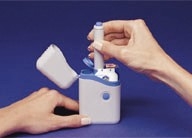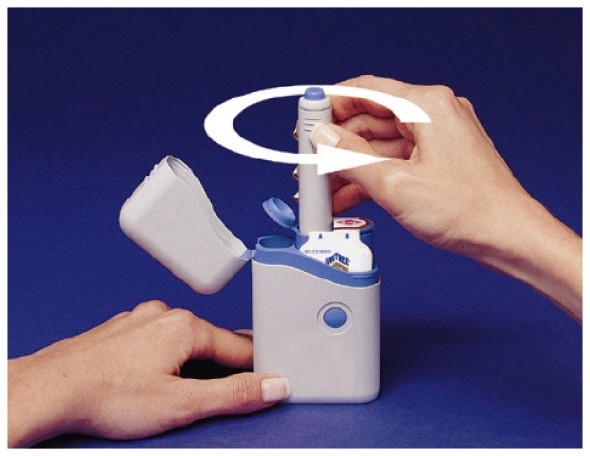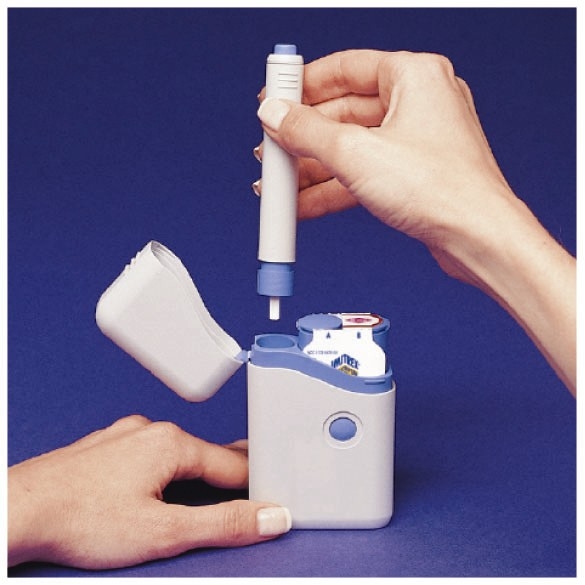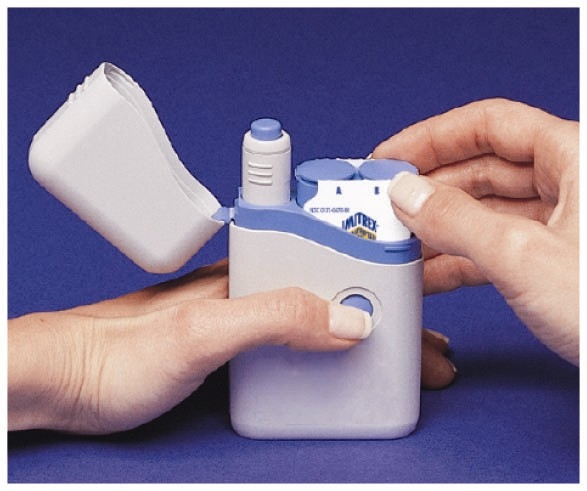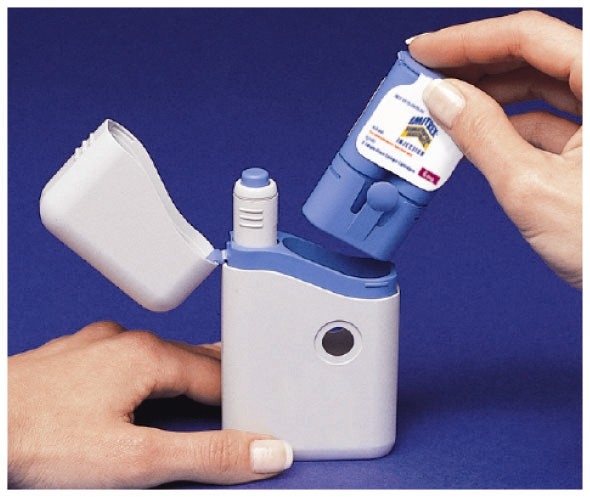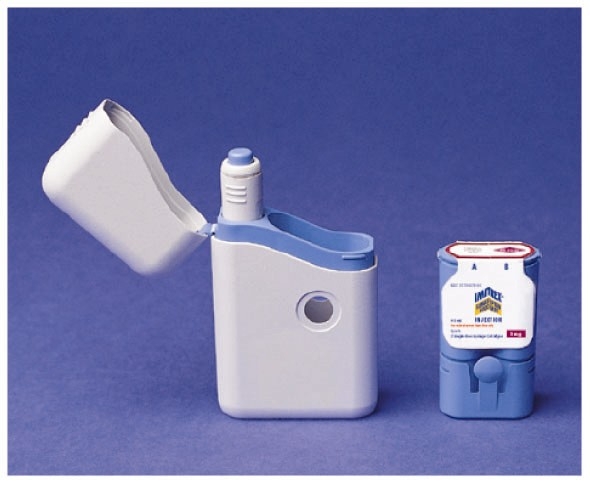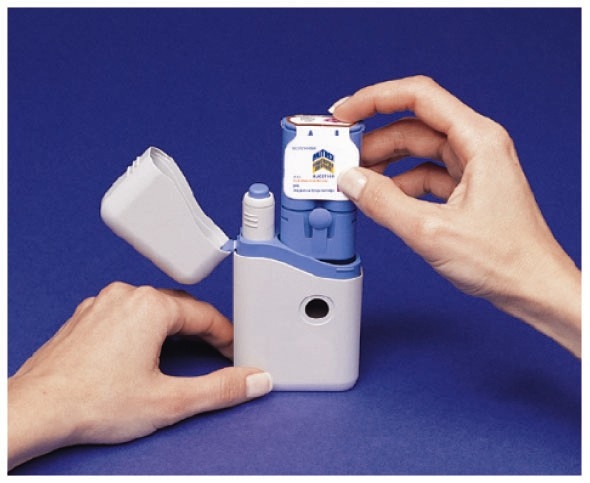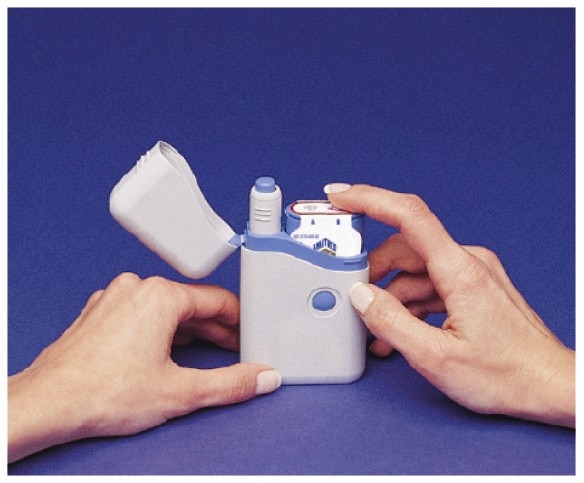 DRUG LABEL: IMITREX
NDC: 54868-3180 | Form: INJECTION
Manufacturer: Physicians Total Care, Inc.
Category: prescription | Type: HUMAN PRESCRIPTION DRUG LABEL
Date: 20111212

ACTIVE INGREDIENTS: SUMATRIPTAN SUCCINATE 6 mg/0.5 mL
INACTIVE INGREDIENTS: SODIUM CHLORIDE 3.5 mg/0.5 mL; WATER

IMITREX®
(sumatriptan succinate)
Injection
For Subcutaneous Use Only.

DESCRIPTION

IMITREX (sumatriptan succinate) Injection is a selective 5-hydroxytryptamine1 receptor subtype agonist. Sumatriptan succinate is chemically designated as 3-[2-(dimethylamino)ethyl]-N-methyl-indole-5-methanesulfonamide succinate (1:1), and it has the following structure:

The empirical formula is C14H21N3O2S•C4H6O4, representing a molecular weight of 413.5.

Sumatriptan succinate is a white to off-white powder that is readily soluble in water and in saline.

IMITREX Injection is a clear, colorless to pale yellow, sterile, nonpyrogenic solution for subcutaneous injection. Each 0.5 mL of IMITREX Injection 8 mg/mL solution contains 4 mg of sumatriptan (base) as the succinate salt and 3.8 mg of sodium chloride, USP in Water for Injection, USP. Each 0.5 mL of IMITREX Injection 12 mg/mL solution contains 6 mg of sumatriptan (base) as the succinate salt and 3.5 mg of sodium chloride, USP in Water for Injection, USP. The pH range of both solutions is approximately 4.2 to 5.3. The osmolality of both injections is 291 mOsmol.

CLINICAL PHARMACOLOGY

Mechanism of Action

Sumatriptan is a selective agonist for a vascular 5-hydroxytryptamine1 receptor subtype (probably a member of the 5-HT1D family) with no significant affinity (as measured using standard radioligand binding assays) or pharmacological activity at 5-HT2, 5-HT3 receptor subtypes or at alpha1-, alpha2-, or beta-adrenergic; dopamine1; dopamine2; muscarinic; or benzodiazepine receptors.

The vascular 5-HT1 receptor subtype to which sumatriptan binds selectively, and through which it presumably exerts its antimigrainous effect, is present on cranial arteries in both dog and primate, on the human basilar artery, and in the vasculature of the isolated dura mater of humans. In these tissues, sumatriptan activates this receptor to cause vasoconstriction, an action in humans correlating with the relief of migraine and cluster headache. In the anesthetized dog, sumatriptan selectively reduces the carotid arterial blood flow with little or no effect on arterial blood pressure or total peripheral resistance. In the cat, sumatriptan selectively constricts the carotid arteriovenous anastomoses while having little effect on blood flow or resistance in cerebral or extracerebral tissues.

Corneal Opacities

Dogs receiving oral sumatriptan developed corneal opacities and defects in the corneal epithelium. Corneal opacities were seen at the lowest dosage tested, 2 mg/kg/day, and were present after 1 month of treatment. Defects in the corneal epithelium were noted in a 60-week study. Earlier examinations for these toxicities were not conducted and no-effect doses were not established; however, the relative exposure at the lowest dose tested was approximately 5 times the human exposure after a 100-mg oral dose or 3 times the human exposure after a 6-mg subcutaneous dose.

Melanin Binding

In rats with a single subcutaneous dose (0.5 mg/kg) of radiolabeled sumatriptan, the elimination half-life of radioactivity from the eye was 15 days, suggesting that sumatriptan and its metabolites bind to the melanin of the eye. The clinical significance of this binding is unknown.

Pharmacokinetics

Pharmacokinetic parameters following a 6-mg subcutaneous injection into the deltoid area of the arm in 9 males (mean age: 33 years, mean weight: 77 kg) were systemic clearance: 1,194 ± 149 mL/min (mean ± S.D.), distribution half-life: 15 ± 2 minutes, terminal half-life: 115 ± 19 minutes, and volume of distribution central compartment: 50 ± 8 liters. Of this dose, 22% ± 4% was excreted in the urine as unchanged sumatriptan and 38% ± 7% as the indole acetic acid metabolite.

After a single 6-mg subcutaneous manual injection into the deltoid area of the arm in 18 healthy males (age: 24 ± 6 years, weight: 70 kg), the maximum serum concentration (Cmax) was (mean ± standard deviation) 74 ± 15 ng/mL and the time to peak concentration (Tmax) was 12 minutes after injection (range: 5 to 20 minutes). In this study, the same dose injected subcutaneously in the thigh gave a Cmax of 61 ± 15 ng/mL by manual injection versus 52 ± 15 ng/mL by autoinjector techniques. The Tmax or amount absorbed was not significantly altered by either the site or technique of injection.

The bioavailability of sumatriptan via subcutaneous site injection to 18 healthy male subjects was 97% ± 16% of that obtained following intravenous injection. Protein binding, determined by equilibrium dialysis over the concentration range of 10 to 1,000 ng/mL, is low, approximately 14% to 21%. The effect of sumatriptan on the protein binding of other drugs has not been evaluated.

Special Populations

Renal Impairment: The effect of renal impairment on the pharmacokinetics of sumatriptan has not been examined, but little clinical effect would be expected as sumatriptan is largely metabolized to an inactive substance.

Hepatic Impairment: The effect of hepatic disease on the pharmacokinetics of subcutaneously and orally administered sumatriptan has been evaluated. There were no statistically significant differences in the pharmacokinetics of subcutaneously administered sumatriptan in hepatically impaired patients compared with healthy controls. However, the liver plays an important role in the presystemic clearance of orally administered sumatriptan. Accordingly, the bioavailability of sumatriptan following oral administration may be markedly increased in patients with liver disease. In 1 small study of hepatically impaired patients (N = 8) matched for sex, age, and weight with healthy subjects, the hepatically impaired patients had an approximately 70% increase in AUC and Cmax and a Tmax 40 minutes earlier compared with the healthy subjects.

Age: The pharmacokinetics of sumatriptan in the elderly (mean age: 72 years, 2 males and 4 females) and in patients with migraine (mean age: 38 years, 25 males and 155 females) were similar to that in healthy male subjects (mean age: 30 years) (see PRECAUTIONS: Geriatric Use).

Race: The systemic clearance and Cmax of sumatriptan were similar in black (n = 34) and Caucasian (n = 38) healthy male subjects.

Drug Interactions

Monoamine Oxidase Inhibitors: In vitro studies with human microsomes suggest that sumatriptan is metabolized by monoamine oxidase (MAO), predominantly the A isoenzyme. In a study of 14 healthy females, pretreatment with MAO-A inhibitor decreased the clearance of sumatriptan. Under the conditions of this experiment, the result was a 2-fold increase in the area under the sumatriptan plasma concentration x time curve (AUC), corresponding to a 40% increase in elimination half-life. No significant effect was seen with an MAO-B inhibitor.

Pharmacodynamics

Typical Physiologic Responses:

Blood Pressure: See WARNINGS: Increase in Blood Pressure.

Peripheral (Small) Arteries: In healthy volunteers (N = 18), a study evaluating the effects of sumatriptan on peripheral (small vessel) arterial reactivity failed to detect a clinically significant increase in peripheral resistance.

Heart Rate: Transient increases in blood pressure observed in some patients in clinical studies carried out during sumatriptan’s development as a treatment for migraine were not accompanied by any clinically significant changes in heart rate.

Respiratory Rate: Experience gained during the clinical development of sumatriptan as a treatment for migraine failed to detect an effect of the drug on respiratory rate.

CLINICAL TRIALS

Migraine

In US controlled clinical trials enrolling more than 1,000 patients during migraine attacks who were experiencing moderate or severe pain and 1 or more of the symptoms enumerated in Table 2, onset of relief began as early as 10 minutes following a 6-mg IMITREX Injection. Smaller doses of sumatriptan may also prove effective, although the proportion of patients obtaining adequate relief is decreased and the latency to that relief is greater.

In 1 well-controlled study where placebo (n = 62) was compared with 6 different doses of IMITREX Injection (n = 30 each group) in a single-attack, parallel-group design, the dose response relationship was found to be as shown in Table 1.

Table 1. Dose Response Relationship for Efficacy
IMITREX Dose (mg) | % Patients With Reliefa at 10 Minutes | % Patients With Reliefa at 30 Minutes | % Patients With Reliefa at 1 Hour | % Patients With Reliefa at 2 Hours | Adverse Events Incidence (%)
Placebo | 5 | 15 | 24 | 21 | 55
1 | 10 | 40 | 43 | 40 | 63
2 | 7 | 23 | 57 | 43 | 63
3 | 17 | 47 | 57 | 60 | 77
4 | 13 | 37 | 50 | 57 | 80
6 | 10 | 63 | 73 | 70 | 83
8 | 23 | 57 | 80 | 83 | 93

aRelief is defined as the reduction of moderate or severe pain to no or mild pain after dosing without use of rescue medication.

In 2 US well-controlled clinical trials in 1,104 migraine patients with moderate or severe migraine pain, the onset of relief was rapid (less than 10 minutes) with IMITREX Injection 6 mg. Headache relief, as evidenced by a reduction in pain from severe or moderately severe to mild or no headache, was achieved in 70% of the patients within 1 hour of a single 6-mg subcutaneous dose of IMITREX Injection. Headache relief was achieved in approximately 82% of patients within 2 hours, and 65% of all patients were pain free within 2 hours.

Table 2 shows the 1- and 2-hour efficacy results for IMITREX Injection 6 mg.

Table 2. Efficacy Data From US Phase III Trials
1-Hour Data | Study 1 |  | Study 2
1-Hour Data | Placebo (n = 190) | IMITREX 6 mg (n = 384) | Placebo (n = 180) | IMITREX 6 mg (n = 350)
Patients with pain relief (grade 0/1) | 18% | 70%a | 26% | 70%a
Patients with no pain | 5% | 48%a | 13% | 49%
Patients without nausea | 48% | 73%a | 50% | 73%a
Patients without photophobia | 23% | 56%a | 25% | 58%*
Patients with little or no clinical disabilityb | 34% | 76%a | 34% | 76%a
2-Hour Data | Study 1 |  | Study 2
2-Hour Data | Placeboc | IMITREX 6 mgd | Placeboc | IMITREX 6 mgd
Patients with pain relief (grade 0/1) | 31% | 81%a | 39% | 82%a
Patients with no pain | 11% | 63%a | 19% | 65%a
Patients without nausea | 56% | 82%a | 63% | 81%a
Patients without photophobia | 31% | 72%a | 35% | 71%a
Patients with little or no clinical disabilityb | 42% | 85%a | 49% | 84%a

ap<0.05 versus placebo.

bA successful outcome in terms of clinical disability was defined prospectively as ability to work mildly impaired or ability to work and function normally.

cIncludes patients that may have received an additional placebo injection 1 hour after the initial injection.

dIncludes patients that may have received an additional 6 mg of IMITREX Injection 1 hour after the initial injection.

IMITREX Injection also relieved photophobia, phonophobia (sound sensitivity), nausea, and vomiting associated with migraine attacks. Similar efficacy was seen when patients self-administered IMITREX Injection using an autoinjector.

The efficacy of IMITREX Injection is unaffected by whether or not migraine is associated with aura, duration of attack, gender or age of the patient, or concomitant use of common migraine prophylactic drugs (e.g., beta-blockers).

Cluster Headache

The efficacy of IMITREX Injection in the acute treatment of cluster headache was demonstrated in 2 randomized, double-blind, placebo-controlled, 2-period crossover trials. Patients age 21 to 65 were enrolled and were instructed to treat a moderate to very severe headache within 10 minutes of onset. Headache relief was defined as a reduction in headache severity to mild or no pain. In both trials, the proportion of individuals gaining relief at 10 or 15 minutes was significantly greater among patients receiving 6 mg of IMITREX Injection compared with those who received placebo (see Table 3). One study evaluated a 12-mg dose; there was no statistically significant difference in outcome between patients randomized to the 6- and 12-mg doses.

Table 3. Efficacy Data From the Pivotal Cluster Headache Studies
 | Study 1 |  | Study 2
 | Placebo (n = 39) | IMITREX 6 mg (n = 39) | Placebo (n = 88) | IMITREX 6 mg (n = 92)
Patients with pain relief (no/mild)
5 minutes postinjection | 8% | 21% | 7% | 23%a
10 minutes postinjection | 10% | 49%a | 25% | 49%
15 minutes postinjection | 26% | 74%a | 35% | 75%a

ap<0.05.

(n = Number of headaches treated.)

The Kaplan-Meier (product limit) Survivorship Plot (Figure 1) provides an estimate of the cumulative probability of a patient with a cluster headache obtaining relief after being treated with either sumatriptan or placebo.

Figure 1. Time to Relief From Time of Injectiona

aPatients taking rescue medication were censored at 15 minutes.

The plot was constructed with data from patients who either experienced relief or did not require (request) rescue medication within a period of 2 hours following treatment. As a consequence, the data in the plot are derived from only a subset of the 258 headaches treated (rescue medication was required in 52 of the 127 placebo-treated headaches and 18 of the 131 sumatriptan-treated headaches).

Other data suggest that treatment with sumatriptan is not associated with an increase in early recurrence of headache and has little effect on the incidence of latter-occurring headaches (i.e., those occurring after 2, but before 18 or 24 hours).

INDICATIONS AND USAGE

IMITREX Injection is indicated for 1) the acute treatment of migraine attacks with or without aura and 2) the acute treatment of cluster headache episodes.

IMITREX Injection is not for use in the management of hemiplegic or basilar migraine (see CONTRAINDICATIONS).

CONTRAINDICATIONS

IMITREX Injection should not be given intravenously because of its potential to cause coronary vasospasm.

IMITREX Injection should not be given to patients with history, symptoms, or signs of ischemic cardiac, cerebrovascular, or peripheral vascular syndromes. In addition, patients with other significant underlying cardiovascular diseases should not receive IMITREX Injection. Ischemic cardiac syndromes include, but are not limited to, angina pectoris of any type (e.g., stable angina of effort, vasospastic forms of angina such as the Prinzmetal variant), all forms of myocardial infarction, and silent myocardial ischemia. Cerebrovascular syndromes include, but are not limited to, strokes of any type as well as transient ischemic attacks. Peripheral vascular disease includes, but is not limited to, ischemic bowel disease (see WARNINGS: Other Vasospasm-Related Events and WARNINGS: Risk of Myocardial Ischemia and/or Infarction and Other Adverse Cardiac Events).

Because IMITREX Injection may increase blood pressure, it should not be given to patients with uncontrolled hypertension.

IMITREX Injection and any ergotamine-containing or ergot-type medication (like dihydroergotamine or methysergide) should not be used within 24 hours of each other, nor should IMITREX Injection and another 5-HT 1 agonist.

IMITREX Injection should not be administered to patients with hemiplegic or basilar migraine.

IMITREX Injection is contraindicated in patients with hypersensitivity to sumatriptan or any of its components.

IMITREX Injection is contraindicated in patients with severe hepatic impairment.

WARNINGS

IMITREX Injection should only be used where a clear diagnosis of migraine or cluster headache has been established. The prescriber should be aware that cluster headache patients often possess one or more predictive risk factors for coronary artery disease (CAD).

Risk of Myocardial Ischemia and/or Infarction and Other Adverse Cardiac Events

Sumatriptan should not be given to patients with documented ischemic or vasospastic CAD (see CONTRAINDICATIONS). It is strongly recommended that sumatriptan not be given to patients in whom unrecognized CAD is predicted by the presence of risk factors (e.g., hypertension, hypercholesterolemia, smoker, obesity, diabetes, strong family history of CAD, female with surgical or physiological menopause, male over 40 years of age) unless a cardiovascular evaluation provides satisfactory clinical evidence that the patient is reasonably free of coronary artery and ischemic myocardial disease or other significant underlying cardiovascular disease. The sensitivity of cardiac diagnostic procedures to detect cardiovascular disease or predisposition to coronary artery vasospasm is modest, at best. If, during the cardiovascular evaluation, the patient’s medical history or electrocardiographic investigations reveal findings indicative of or consistent with coronary artery vasospasm or myocardial ischemia, sumatriptan should not be administered (see CONTRAINDICATIONS).

For patients with risk factors predictive of CAD who are determined to have a satisfactory cardiovascular evaluation, it is strongly recommended that administration of the first dose of sumatriptan injection take place in the setting of a physician’s office or similar medically staffed and equipped facility. Because cardiac ischemia can occur in the absence of clinical symptoms, consideration should be given to obtaining an electrocardiogram (ECG) during the interval immediately following the first dose in these patients with risk factors.

It is recommended that patients who are intermittent long-term users of sumatriptan and who have or acquire risk factors predictive of CAD, as described above, undergo periodic interval cardiovascular evaluation as they continue to use sumatriptan. In considering this recommendation for periodic cardiovascular evaluation, it is noted that patients with cluster headache are predominantly male and over 40 years of age, which are risk factors for CAD.

The systematic approach described above is intended to reduce the likelihood that patients with unrecognized cardiovascular disease will be inadvertently exposed to sumatriptan.

Drug-Associated Cardiac Events and Fatalities

Serious adverse cardiac events, including acute myocardial infarction, life-threatening disturbances of cardiac rhythm, and death have been reported within a few hours following the administration of IMITREX Injection or IMITREX® (sumatriptan succinate) Tablets. Considering the extent of use of sumatriptan in patients with migraine, the incidence of these events is extremely low.

The fact that sumatriptan can cause coronary vasospasm, that some of these events have occurred in patients with no prior cardiac disease history and with documented absence of CAD, and the close proximity of the events to sumatriptan use support the conclusion that some of these cases were caused by the drug. In many cases, however, where there has been known underlying CAD, the relationship is uncertain.

Premarketing Experience With Sumatriptan: Among the more than 1,900 patients with migraine who participated in premarketing controlled clinical trials of subcutaneous sumatriptan, there were 8 patients who sustained clinical events during or shortly after receiving sumatriptan that may have reflected coronary artery vasospasm. Six of these 8 patients had ECG changes consistent with transient ischemia, but without accompanying clinical symptoms or signs. Of these 8 patients, 4 had either findings suggestive of CAD or risk factors predictive of CAD prior to study enrollment.

Of 6,348 patients with migraine who participated in premarketing controlled and uncontrolled clinical trials of oral sumatriptan, 2 experienced clinical adverse events shortly after receiving oral sumatriptan that may have reflected coronary vasospasm. Neither of these adverse events was associated with a serious clinical outcome.

Among approximately 4,000 patients with migraine who participated in premarketing controlled and uncontrolled clinical trials of sumatriptan nasal spray, 1 patient experienced an asymptomatic subendocardial infarction possibly subsequent to a coronary vasospastic event.

Postmarketing Experience With Sumatriptan: Serious cardiovascular events, some resulting in death, have been reported in association with the use of IMITREX Injection or IMITREX Tablets. The uncontrolled nature of postmarketing surveillance, however, makes it impossible to determine definitively the proportion of the reported cases that were actually caused by sumatriptan or to reliably assess causation in individual cases. On clinical grounds, the longer the latency between the administration of IMITREX and the onset of the clinical event, the less likely the association is to be causative. Accordingly, interest has focused on events beginning within 1 hour of the administration of IMITREX.

Cardiac events that have been observed to have onset within 1 hour of sumatriptan administration include: coronary artery vasospasm, transient ischemia, myocardial infarction, ventricular tachycardia and ventricular fibrillation, cardiac arrest, and death.

Some of these events occurred in patients who had no findings of CAD and appear to represent consequences of coronary artery vasospasm. However, among domestic reports of serious cardiac events within 1 hour of sumatriptan administration, the majority had risk factors predictive of CAD and the presence of significant underlying CAD was established in most cases (see CONTRAINDICATIONS).

Drug-Associated Cerebrovascular Events and Fatalities

Cerebral hemorrhage, subarachnoid hemorrhage, stroke, and other cerebrovascular events have been reported in patients treated with oral or subcutaneous sumatriptan, and some have resulted in fatalities. The relationship of sumatriptan to these events is uncertain. In a number of cases, it appears possible that the cerebrovascular events were primary, sumatriptan having been administered in the incorrect belief the symptoms experienced were a consequence of migraine when they were not. As with other acute migraine therapies, before treating headaches in patients not previously diagnosed as migraineurs, and in migraineurs who present with atypical symptoms, care should be taken to exclude other potentially serious neurological conditions. It should also be noted that patients with migraine may be at increased risk of certain cerebrovascular events (e.g., cerebrovascular accident, transient ischemic attack).

Other Vasospasm-Related Events

Sumatriptan may cause vasospastic reactions other than coronary artery vasospasm. Both peripheral vascular ischemia and colonic ischemia with abdominal pain and bloody diarrhea have been reported. Very rare reports of transient and permanent blindness and significant partial vision loss have been reported with the use of sumatriptan. Visual disorders may also be part of a migraine attack.

Serotonin Syndrome

The development of a potentially life-threatening serotonin syndrome may occur with triptans, including treatment with IMITREX, particularly during combined use with selective serotonin reuptake inhibitors (SSRIs) or serotonin norepinephrine reuptake inhibitors (SNRIs). If concomitant treatment with sumatriptan and an SSRI (e.g., fluoxetine, paroxetine, sertraline, fluvoxamine, citalopram, escitalopram) or SNRI (e.g., venlafaxine, duloxetine) is clinically warranted, careful observation of the patient is advised, particularly during treatment initiation and dose increases. Serotonin syndrome symptoms may include mental status changes (e.g., agitation, hallucinations, coma), autonomic instability (e.g., tachycardia, labile blood pressure, hyperthermia), neuromuscular aberrations (e.g., hyperreflexia, incoordination), and/or gastrointestinal symptoms (e.g., nausea, vomiting, diarrhea).

Increase in Blood Pressure

Significant elevation in blood pressure, including hypertensive crisis, has been reported on rare occasions in patients with and without a history of hypertension. Sumatriptan is contraindicated in patients with uncontrolled hypertension (see CONTRAINDICATIONS). Sumatriptan should be administered with caution to patients with controlled hypertension as transient increases in blood pressure and peripheral vascular resistance have been observed in a small proportion of patients.

Concomitant Drug Use

In patients taking MAO-A inhibitors, sumatriptan plasma levels attained after treatment with recommended doses are nearly double those obtained under other conditions. Accordingly, the coadministration of sumatriptan and an MAO-A inhibitor is not generally recommended. If such therapy is clinically warranted, however, suitable dose adjustment and appropriate observation of the patient is advised (see CLINICAL PHARMACOLOGY: Drug Interactions: Monoamine Oxidase Inhibitors).

Use in Women of Childbearing Potential

See PRECAUTIONS: Pregnancy.

Hypersensitivity

Hypersensitivity (anaphylaxis/anaphylactoid) reactions have occurred on rare occasions in patients receiving sumatriptan. Such reactions can be life threatening or fatal. In general, hypersensitivity reactions to drugs are more likely to occur in individuals with a history of sensitivity to multiple allergens (see CONTRAINDICATIONS).

PRECAUTIONS

General

Chest, jaw, or neck tightness is relatively common after administration of IMITREX Injection. Chest discomfort and jaw or neck tightness have been reported following use of IMITREX Tablets and have also been reported infrequently following the administration of IMITREX® (sumatriptan) Nasal Spray. Only rarely have these symptoms been associated with ischemic ECG changes. However, because sumatriptan may cause coronary artery vasospasm, patients who experience signs or symptoms suggestive of angina following sumatriptan should be evaluated for the presence of CAD or a predisposition to Prinzmetal variant angina before receiving additional doses of sumatriptan and should be monitored electrocardiographically if dosing is resumed and similar symptoms recur. Similarly, patients who experience other symptoms or signs suggestive of decreased arterial flow, such as ischemic bowel syndrome or Raynaud syndrome, following sumatriptan should be evaluated for atherosclerosis or predisposition to vasospasm (see WARNINGS: Risk of Myocardial Ischemia and/or Infarction and Other Adverse Cardiac Events and WARNINGS: Other Vasospasm-Related Events).

IMITREX should also be administered with caution to patients with diseases that may alter the absorption, metabolism, or excretion of drugs, such as impaired hepatic or renal function.

There have been rare reports of seizure following administration of sumatriptan. Sumatriptan should be used with caution in patients with a history of epilepsy or conditions associated with a lowered seizure threshold.

Care should be taken to exclude other potentially serious neurologic conditions before treating headache in patients not previously diagnosed with migraine or cluster headache or who experience a headache that is atypical for them. There have been rare reports where patients received sumatriptan for severe headaches that were subsequently shown to have been secondary to an evolving neurologic lesion (see WARNINGS: Drug-Associated Cerebrovascular Events and Fatalities). For a given attack, if a patient does not respond to the first dose of sumatriptan, the diagnosis of migraine or cluster headache should be reconsidered before administration of a second dose.

Overuse of acute migraine treatments has been associated with the exacerbation of headache (medication overuse headache) in susceptible patients. Withdrawal of the treatment may be necessary.

Binding to Melanin-Containing Tissues

Because sumatriptan binds to melanin, it could accumulate in melanin-rich tissues (such as the eye) over time. This raises the possibility that sumatriptan could cause toxicity in these tissues after extended use. However, no effects on the retina related to treatment with sumatriptan were noted in any of the toxicity studies. Although no systematic monitoring of ophthalmologic function was undertaken in clinical trials, and no specific recommendations for ophthalmologic monitoring are offered, prescribers should be aware of the possibility of long-term ophthalmologic effects (see CLINICAL PHARMACOLOGY: Melanin Binding).

Corneal Opacities

Sumatriptan causes corneal opacities and defects in the corneal epithelium in dogs; this raises the possibility that these changes may occur in humans. While patients were not systematically evaluated for these changes in clinical trials, and no specific recommendations for monitoring are being offered, prescribers should be aware of the possibility of these changes (see CLINICAL PHARMACOLOGY: Corneal Opacities).

Patients who are advised to self-administer IMITREX Injection in medically unsupervised situations should receive instruction on the proper use of the product from the physician or other suitably qualified health care professional prior to doing so for the first time.

Information for Patients

With the autoinjector, the needle penetrates approximately 1/4 of an inch (5 to 6 mm). Since the injection is intended to be given subcutaneously, intramuscular or intravascular delivery should be avoided. Patients should be directed to use injection sites with an adequate skin and subcutaneous thickness to accommodate the length of the needle. See PATIENT INFORMATION at the end of this labeling for the text of the separate leaflet provided for patients.

Patients should be cautioned about the risk of serotonin syndrome with the use of sumatriptan or other triptans, especially during combined use with SSRIs or SNRIs.

Laboratory Tests

No specific laboratory tests are recommended for monitoring patients prior to and/or after treatment with sumatriptan.

Drug Interactions

Selective Serotonin Reuptake Inhibitors/Serotonin Norepinephrine Reuptake Inhibitors and Serotonin Syndrome: Cases of life-threatening serotonin syndrome have been reported during combined use of SSRIs or SNRIs and triptans (see WARNINGS).

Migraine Prophylactic Medications: There is no evidence that concomitant use of migraine prophylactic medications has any effect on the efficacy of sumatriptan. In 2 Phase III trials in the US, a retrospective analysis of 282 patients who had been using prophylactic drugs (verapamil n = 63, amitriptyline n = 57, propranolol n = 94, for 45 other drugs n = 123) were compared with those who had not used prophylaxis (N = 452). There were no differences in relief rates at 60 minutes postdose for IMITREX Injection, whether or not prophylactic medications were used.

Ergot-Containing Drugs: Ergot-containing drugs have been reported to cause prolonged vasospastic reactions. Because there is a theoretical basis that these effects may be additive, use of ergotamine-containing or ergot-type medications (like dihydroergotamine or methysergide) and sumatriptan within 24 hours of each other should be avoided (see CONTRAINDICATIONS).

Monoamine Oxidase-A Inhibitors: MAO-A inhibitors reduce sumatriptan clearance, significantly increasing systemic exposure. Therefore, the use of sumatriptan in patients receiving MAO-A inhibitors is not ordinarily recommended. If the clinical situation warrants the combined use of sumatriptan and an MAOI, the dose of sumatriptan employed should be reduced (see CLINICAL PHARMACOLOGY: Drug Interactions: Monoamine Oxidase Inhibitors and WARNINGS: Concomitant Drug Use).

Drug/Laboratory Test Interactions

IMITREX is not known to interfere with commonly employed clinical laboratory tests.

Carcinogenesis, Mutagenesis, Impairment of Fertility

In carcinogenicity studies, rats and mice were given sumatriptan by oral gavage (rats: 104 weeks) or drinking water (mice: 78 weeks). Average exposures achieved in mice receiving the highest dose were approximately 110 times the exposure attained in humans after the maximum recommended single dose of 6 mg. The highest dose to rats was approximately 260 times the maximum single dose of 6 mg on a mg/m^2 basis. There was no evidence of an increase in tumors in either species related to sumatriptan administration.

Sumatriptan was not mutagenic in the presence or absence of metabolic activation when tested in 2 gene mutation assays (the Ames test and the in vitro mammalian Chinese hamster V79/HGPRT assay). In 2 cytogenetics assays (the in vitro human lymphocyte assay and the in vivo rat micronucleus assay) sumatriptan was not associated with clastogenic activity.

A fertility study (Segment I) by the subcutaneous route, during which male and female rats were dosed daily with sumatriptan prior to and throughout the mating period, has shown no evidence of impaired fertility at doses equivalent to approximately 100 times the maximum recommended single human dose of 6 mg on a mg/m^2 basis. However, following oral administration, a treatment-related decrease in fertility, secondary to a decrease in mating, was seen for rats treated with 50 and 500 mg/kg/day. The no-effect dose for this finding was approximately 8 times the maximum recommended single human dose of 6 mg on a mg/m^2 basis. It is not clear whether the problem is associated with the treatment of males or females or both.

Pregnancy

Pregnancy Category C. Sumatriptan has been shown to be embryolethal in rabbits when given daily at a dose approximately equivalent to the maximum recommended single human subcutaneous dose of 6 mg on a mg/m^2 basis. There is no evidence that establishes that sumatriptan is a human teratogen; however, there are no adequate and well-controlled studies in pregnant women. IMITREX Injection should be used during pregnancy only if the potential benefit justifies the potential risk to the fetus.

In assessing this information, the following additional findings should be considered.

Embryolethality: When given intravenously to pregnant rabbits daily throughout the period of organogenesis, sumatriptan caused embryolethality at doses at or close to those producing maternal toxicity. The mechanism of the embryolethality is not known. These doses were approximately equivalent to the maximum single human dose of 6 mg on a mg/m^2 basis.

The intravenous administration of sumatriptan to pregnant rats throughout organogenesis at doses that are approximately 20 times a human dose of 6 mg on a mg/m^2 basis, did not cause embryolethality. Additionally, in a study of pregnant rats given subcutaneous sumatriptan daily prior to and throughout pregnancy, there was no evidence of increased embryo/fetal lethality.

Teratogenicity: Term fetuses from Dutch Stride rabbits treated during organogenesis with oral sumatriptan exhibited an increased incidence of cervicothoracic vascular and skeletal abnormalities. The functional significance of these abnormalities is not known. The highest no-effect dose for these effects was 15 mg/kg/day, approximately 50 times the maximum single dose of 6 mg on a mg/m^2 basis.

In a study in rats dosed daily with subcutaneous sumatriptan prior to and throughout pregnancy, there was no evidence of teratogenicity.

Pregnancy Registry: To monitor fetal outcomes of pregnant women exposed to IMITREX, GlaxoSmithKline maintains a Sumatriptan Pregnancy Registry. Physicians are encouraged to register patients by calling (800) 336-2176.

Nursing Mothers

Sumatriptan is excreted in human breast milk following subcutaneous administration. Infant exposure to sumatriptan can be minimized by avoiding breastfeeding for 12 hours after treatment with IMITREX Injection.

Pediatric Use

Safety and effectiveness of IMITREX Injection in pediatric patients under 18 years of age have not been established; therefore, IMITREX Injection is not recommended for use in patients under 18 years of age.

Two controlled clinical trials evaluated sumatriptan nasal spray (5 to 20 mg) in 1,248 adolescent migraineurs aged 12 to 17 years who treated a single attack. The studies did not establish the efficacy of sumatriptan nasal spray compared with placebo in the treatment of migraine in adolescents. Adverse events observed in these clinical trials were similar in nature to those reported in clinical trials in adults.

Five controlled clinical trials (2 single-attack studies, 3 multiple-attack studies) evaluating oral sumatriptan (25 to 100 mg) in pediatric patients aged 12 to 17 years enrolled a total of 701 adolescent migraineurs. These studies did not establish the efficacy of oral sumatriptan compared with placebo in the treatment of migraine in adolescents. Adverse events observed in these clinical trials were similar in nature to those reported in clinical trials in adults. The frequency of all adverse events in these patients appeared to be both dose- and age-dependent, with younger patients reporting events more commonly than older adolescents.

Postmarketing experience documents that serious adverse events have occurred in the pediatric population after use of subcutaneous, oral, and/or intranasal sumatriptan. These reports include events similar in nature to those reported rarely in adults, including stroke, visual loss, and death. A myocardial infarction has been reported in a 14-year-old male following the use of oral sumatriptan; clinical signs occurred within 1 day of drug administration. Since clinical data to determine the frequency of serious adverse events in pediatric patients who might receive injectable, oral, or intranasal sumatriptan are not presently available, the use of sumatriptan in patients aged younger than 18 years is not recommended.

Geriatric Use

The use of sumatriptan in elderly patients is not recommended because elderly patients are more likely to have decreased hepatic function, they are at higher risk for CAD, and blood pressure increases may be more pronounced in the elderly (see WARNINGS: Risk of Myocardial Ischemia and/or Infarction and Other Adverse Cardiac Events).

ADVERSE REACTIONS

Serious cardiac events, including some that have been fatal, have occurred following the use of IMITREX Injection or Tablets. These events are extremely rare and most have been reported in patients with risk factors predictive of CAD. Events reported have included coronary artery vasospasm, transient myocardial ischemia, myocardial infarction, ventricular tachycardia, and ventricular fibrillation (see CONTRAINDICATIONS, WARNINGS: Risk of Myocardial Ischemia and/or Infarction and Other Adverse Cardiac Events, and PRECAUTIONS: General).

Significant hypertensive episodes, including hypertensive crises, have been reported on rare occasions in patients with or without a history of hypertension (see WARNINGS: Increase in Blood Pressure).

Among patients in clinical trials of subcutaneous IMITREX Injection (N = 6,218), up to 3.5% of patients withdrew for reasons related to adverse events.

Incidence in Controlled Clinical Trials of Migraine Headache

Table 4 lists adverse events that occurred in 2 large US, Phase III, placebo-controlled clinical trials in migraine patients following either a single 6-mg dose of IMITREX Injection or placebo. Only events that occurred at a frequency of 2% or more in groups treated with IMITREX Injection 6 mg and occurred at a frequency greater than the placebo group are included in Table 4.

Table 4. Treatment Emergent Adverse Experience Incidence in 2 Large Placebo-Controlled Migraine Clinical Trials: Events Reported by at Least 2% of Patients Treated With IMITREX Injection 6 mga
Adverse Event | Percent of Patients Reporting
Adverse Event | IMITREX Injection; 6 mg Subcutaneous; (n = 547) | Placebo; (n = 370)
Atypical sensations | 42 | 9
Tingling | 14 | 3
Warm/hot sensation | 11 | 4
Burning sensation | 7 | <1
Feeling of heaviness | 7 | 1
Pressure sensation | 7 | 2
Feeling of tightness | 5 | <1
Numbness | 5 | 2
Feeling strange | 2 | <1
Tight feeling in head | 2 | <1
Cardiovascular
Flushing | 7 | 2
Chest discomfort | 5 | 1
Tightness in chest | 3 | <1
Pressure in chest | 2 | <1
Ear, nose, and throat
Throat discomfort | 3 | <1
Discomfort: nasal cavity/sinuses | 2 | <1
Injection site reaction | 59 | 24
Miscellaneous
Jaw discomfort | 2 | 0
Musculoskeletal
Weakness | 5 | <1
Neck pain/stiffness | 5 | <1
Myalgia | 2 | <1
Neurological
Dizziness/vertigo | 12 | 4
Drowsiness/sedation | 3 | 2
Headache | 2 | <1
Skin
Sweating | 2 | 1

aThe sum of the percentages cited is greater than 100% because patients may experience more than 1 type of adverse event. Only events that occurred at a frequency of 2% or more in groups treated with IMITREX Injection and occurred at a frequency greater than the placebo groups are included.

The incidence of adverse events in controlled clinical trials was not affected by gender or age of the patients. There were insufficient data to assess the impact of race on the incidence of adverse events.

Incidence in Controlled Trials of Cluster Headache

In the controlled clinical trials assessing sumatriptan’s efficacy as a treatment for cluster headache, no new significant adverse events associated with the use of sumatriptan were detected that had not already been identified in association with the drug’s use in migraine.

Overall, the frequency of adverse events reported in the studies of cluster headache were generally lower. Exceptions include reports of paresthesia (5% IMITREX, 0% placebo), nausea and vomiting (4% IMITREX, 0% placebo), and bronchospasm (1% IMITREX, 0% placebo).

Other Events Observed in Association With the Administration of IMITREX Injection

In the paragraphs that follow, the frequencies of less commonly reported adverse clinical events are presented. Because the reports include events observed in open and uncontrolled studies, the role of IMITREX Injection in their causation cannot be reliably determined. Furthermore, variability associated with adverse event reporting, the terminology used to describe adverse events, etc., limit the value of the quantitative frequency estimates provided.

Event frequencies are calculated as the number of patients reporting an event divided by the total number of patients (N = 6,218) exposed to subcutaneous IMITREX Injection. All reported events are included except those already listed in the previous table, those too general to be informative, and those not reasonably associated with the use of the drug. Events are further classified within body system categories and enumerated in order of decreasing frequency using the following definitions: frequent adverse events are defined as those occurring in at least 1/100 patients, infrequent adverse events are those occurring in 1/100 to 1/1,000 patients, and rare adverse events are those occurring in fewer than 1/1,000 patients.

Cardiovascular: Infrequent were hypertension, hypotension, bradycardia, tachycardia, palpitations, pulsating sensations, various transient ECG changes (nonspecific ST or T wave changes, prolongation of PR or QTc intervals, sinus arrhythmia, nonsustained ventricular premature beats, isolated junctional ectopic beats, atrial ectopic beats, delayed activation of the right ventricle), and syncope. Rare were pallor, arrhythmia, abnormal pulse, vasodilatation, and Raynaud syndrome.

Endocrine and Metabolic: Infrequent was thirst. Rare were polydipsia and dehydration.

Eye: Frequent was vision alterations. Infrequent was irritation of the eye.

Gastrointestinal: Frequent were abdominal discomfort and dysphagia. Infrequent were gastroesophageal reflux and diarrhea. Rare were peptic ulcer, retching, flatulence/eructation, and gallstones.

Musculoskeletal: Frequent were muscle cramps. Infrequent were various joint disturbances (pain, stiffness, swelling, ache). Rare were muscle stiffness, need to flex calf muscles, backache, muscle tiredness, and swelling of the extremities.

Neurological: Frequent was anxiety. Infrequent were mental confusion, euphoria, agitation, relaxation, chills, sensation of lightness, tremor, shivering, disturbances of taste, prickling sensations, paresthesia, stinging sensations, facial pain, photophobia, and lacrimation. Rare were transient hemiplegia, hysteria, globus hystericus, intoxication, depression, myoclonia, monoplegia/diplegia, sleep disturbance, difficulties in concentration, disturbances of smell, hyperesthesia, dysesthesia, simultaneous hot and cold sensations, tickling sensations, dysarthria, yawning, reduced appetite, hunger, and dystonia.

Respiratory: Infrequent was dyspnea. Rare were influenza, diseases of the lower respiratory tract, and hiccoughs.

Skin: Infrequent were erythema, pruritus, and skin rashes and eruptions. Rare was skin tenderness.

Urogenital: Rare were dysuria, frequency, dysmenorrhea, and renal calculus.

Miscellaneous: Infrequent were miscellaneous laboratory abnormalities, including minor disturbances in liver function tests, “serotonin agonist effect,” and hypersensitivity to various agents. Rare was fever.

Other Events Observed in the Clinical Development of IMITREX

The following adverse events occurred in clinical trials with IMITREX Tablets and IMITREX Nasal Spray. Because the reports include events observed in open and uncontrolled studies, the role of IMITREX in their causation cannot be reliably determined. All reported events are included except those already listed, those too general to be informative, and those not reasonably associated with the use of the drug.

Breasts: Breast swelling, cysts, disorder of breasts, lumps, masses of breasts, nipple discharge, primary malignant breast neoplasm, and tenderness.

Cardiovascular: Abdominal aortic aneurysm, angina, atherosclerosis, cerebral ischemia, cerebrovascular lesion, heart block, peripheral cyanosis, phlebitis, thrombosis, and transient myocardial ischemia.

Ear, Nose, and Throat: Allergic rhinitis; disorder of nasal cavity/sinuses; ear, nose, and throat hemorrhage; ear infection; external otitis; feeling of fullness in the ear(s); hearing disturbances; hearing loss; Meniere disease; nasal inflammation; otalgia; sensitivity to noise; sinusitis; tinnitus; and upper respiratory inflammation.

Endocrine and Metabolic: Elevated thyrotropin stimulating hormone (TSH) levels; endocrine cysts, lumps, and masses; fluid disturbances; galactorrhea; hyperglycemia; hypoglycemia; hypothyroidism; weight gain; and weight loss.

Eye: Accommodation disorders, blindness and low vision, conjunctivitis, disorders of sclera, external ocular muscle disorders, eye edema and swelling, eye hemorrhage, eye itching, eye pain, keratitis, mydriasis, and visual disturbances.

Gastrointestinal: Abdominal distention, colitis, constipation, dental pain, dyspeptic symptoms, feelings of gastrointestinal pressure, gastric symptoms, gastritis, gastroenteritis, gastrointestinal bleeding, gastrointestinal pain, hematemesis, hypersalivation, hyposalivation, intestinal obstruction, melena, nausea and/or vomiting, oral itching and irritation, pancreatitis, salivary gland swelling, and swallowing disorders.

Hematological Disorders: Anemia.

Mouth and Teeth: Disorder of mouth and tongue (e.g., burning of tongue, numbness of tongue, dry mouth).

Musculoskeletal: Acquired musculoskeletal deformity, arthralgia and articular rheumatitis, arthritis, intervertebral disc disorder, muscle atrophy, muscle tightness and rigidity, musculoskeletal inflammation, and tetany.

Neurological: Apathy, aggressiveness, bad/unusual taste, bradylogia, cluster headache, convulsions, depressive disorders, detachment, disturbance of emotions, drug abuse, facial paralysis, hallucinations, heat sensitivity, incoordination, increased alertness, memory disturbance, migraine, motor dysfunction, neoplasm of pituitary, neuralgia, neurotic disorders, paralysis, personality change, phobia, phonophobia, psychomotor disorders, radiculopathy, raised intracranial pressure, rigidity, stress, syncope, suicide, and twitching.

Respiratory: Asthma, breathing disorders, bronchitis, cough, and lower respiratory tract infection.

Skin: Dry/scaly skin, eczema, herpes, seborrheic dermatitis, skin nodules, tightness of skin, and wrinkling of skin.

Urogenital: Abnormal menstrual cycle, abortion, bladder inflammation, endometriosis, hematuria, increased urination, inflammation of fallopian tubes, intermenstrual bleeding, menstruation symptoms, micturition disorders, urethritis, and urinary infections.

Miscellaneous: Contusions, difficulty in walking, edema, hematoma, hypersensitivity, fever, fluid retention, lymphadenopathy, overdose, speech disturbance, swelling of extremities, swelling of face, and voice disturbances.

Pain and Other Pressure Sensations: Chest pain and/or heaviness, neck/throat/jaw pain/tightness/pressure, and pain (location specified).

Postmarketing Experience (Reports for Subcutaneous or Oral Sumatriptan)

The following section enumerates potentially important adverse events that have occurred in clinical practice and that have been reported spontaneously to various surveillance systems. The events enumerated represent reports arising from both domestic and nondomestic use of oral or subcutaneous dosage forms of sumatriptan. The events enumerated include all except those already listed in the ADVERSE REACTIONS section above or those too general to be informative. Because the reports cite events reported spontaneously from worldwide postmarketing experience, frequency of events and the role of IMITREX Injection in their causation cannot be reliably determined. It is assumed, however, that systemic reactions following sumatriptan use are likely to be similar regardless of route of administration.

Blood: Hemolytic anemia, pancytopenia, thrombocytopenia.

Cardiovascular: Atrial fibrillation, cardiomyopathy, colonic ischemia (see WARNINGS), Prinzmetal variant angina, pulmonary embolism, shock, thrombophlebitis.

Ear, Nose, and Throat: Deafness.

Eye: Ischemic optic neuropathy, retinal artery occlusion, retinal vein thrombosis, loss of vision.

Gastrointestinal: Ischemic colitis with rectal bleeding (see WARNINGS), xerostomia.

Hepatic: Elevated liver function tests.

Neurological: Central nervous system vasculitis, cerebrovascular accident, dysphasia, serotonin syndrome, subarachnoid hemorrhage.

Non-Site Specific: Angioneurotic edema, cyanosis, death (see WARNINGS), temporal arteritis.

Psychiatry: Panic disorder.

Respiratory: Bronchospasm in patients with and without a history of asthma.

Skin: Exacerbation of sunburn, hypersensitivity reactions (allergic vasculitis, erythema, pruritus, rash, shortness of breath, urticaria; in addition, severe anaphylaxis/anaphylactoid reactions have been reported [see WARNINGS: Hypersensitivity]), photosensitivity. Following subcutaneous administration of sumatriptan, pain, redness, stinging, induration, swelling, contusion, subcutaneous bleeding, and, on rare occasions, lipoatrophy (depression in the skin) or lipohypertrophy (enlargement or thickening of tissue) have been reported.

Urogenital: Acute renal failure.

DRUG ABUSE AND DEPENDENCE

The abuse potential of IMITREX Injection cannot be fully delineated in advance of extensive marketing experience. One clinical study enrolling 12 patients with a history of substance abuse failed to induce subjective behavior and/or physiologic response ordinarily associated with drugs that have an established potential for abuse.

OVERDOSAGE

Patients (N = 269) have received single injections of 8 to 12 mg without significant adverse effects. Volunteers (N = 47) have received single subcutaneous doses of up to 16 mg without serious adverse events.

No gross overdoses in clinical practice have been reported. Coronary vasospasm was observed after intravenous administration of IMITREX Injection (see CONTRAINDICATIONS). Overdoses would be expected from animal data (dogs at 0.1 g/kg, rats at 2 g/kg) to possibly cause convulsions, tremor, inactivity, erythema of the extremities, reduced respiratory rate, cyanosis, ataxia, mydriasis, injection site reactions (desquamation, hair loss, and scab formation), and paralysis. The half-life of elimination of sumatriptan is about 2 hours (see CLINICAL PHARMACOLOGY: Pharmacokinetics), and therefore monitoring of patients after overdose with IMITREX Injection should continue while symptoms or signs persist, and for at least 10 hours.

It is unknown what effect hemodialysis or peritoneal dialysis has on the serum concentrations of sumatriptan.

DOSAGE AND ADMINISTRATION

The maximum single recommended adult dose of IMITREX Injection is 6 mg injected subcutaneously. If side effects are dose limiting, then lower doses may be used (see Table 1).

The maximum recommended dose that may be given in 24 hours is two 6-mg injections separated by at least 1 hour. Controlled clinical trials have failed to show that clear benefit is associated with the administration of a second 6-mg dose in patients who have failed to respond to a first injection.

In patients receiving MAO inhibitors, decreased doses of sumatriptan should be considered (see WARNINGS: Concomitant Drug Use and CLINICAL PHARMACOLOGY: Drug Interactions: Monoamine Oxidase Inhibitors).

An autoinjection device is available for use with the 4- and 6-mg prefilled syringe cartridges to facilitate self-administration in patients using the 4- or 6-mg dose. With this device, the needle penetrates approximately 1/4 inch (5 to 6 mm). Since the injection is intended to be given subcutaneously, intramuscular or intravascular delivery should be avoided. Patients should be directed to use injection sites with an adequate skin and subcutaneous thickness to accommodate the length of the needle.

In patients receiving doses other than 4 or 6 mg, only the 6-mg single-dose vial dosage form should be used. Parenteral drug products should be inspected visually for particulate matter and discoloration before administration whenever solution and container permit.

HOW SUPPLIED

IMITREX Injection contains sumatriptan (base) as the succinate salt and is supplied as a clear, colorless to pale yellow, sterile, nonpyrogenic solution as follows:

(NDC 54868-3180-0) IMITREX STATdose System, 6 mg, containing 2 prefilled single-dose syringe cartridges, 1 IMITREX STATdose Pen, 1 carrying case, and a patient information leaflet with instructions for use.

Store between 2° and 30°C (36° and 86°F). Protect from light.

IMITREX, IMITREX STATdose System, and IMITREX STATdose Pen are registered trademarks of GlaxoSmithKline.

This product's prescribing information may have been updated. Please refer to ww.gsk.com for the most current version.

GlaxoSmithKline

Research Triangle Park, NC 27709

©2010, GlaxoSmithKline. All rights reserved.

February 2010

IMJ:3PI

Additional barcode label applied by:
Physicians Total Care, Inc.
Tulsa, Oklahoma 74146

PATIENT INFORMATION

The following wording is contained in a separate leaflet provided for patients.

Read this leaflet carefully several times before you start to use the IMITREX STATdose System. If you have any questions, ask your healthcare provider.

Keep the IMITREX STATdose System out of the reach of children.

Before you use the IMITREX STATdose System

When you first open the IMITREX STATdose System box, the Cartridge Pack and the IMITREX STATdose Pen® are already in the Carrying Case for your convenience.

The grey and blue Carrying Case is used for storing the unloaded Pen and the Cartridge Pack when they are not being used.

The Cartridge Pack holds 2 individually sealed Syringe Cartridges. Each Syringe Cartridge holds 1 dose of IMITREX® (sumatriptan succinate) Injection. The Cartridge Pack for the 4-mg strength of this medicine is yellow, and the Cartridge Pack for the 6-mg strength is blue (as shown). Refill Cartridge Packs are available.

The grey and blue Pen is used to automatically inject 1 dose of medicine from a Syringe Cartridge. Do not touch the Blue Button until you have pressed the Pen against your skin to give a dose. If you press it at any other time, you might lose a dose. The Safety Catch keeps the Pen from accidentally firing until you are ready. The Pen will only work when you slide the grey part of the barrel down to the blue part. Always check to make sure that the white Priming Rod is not sticking out from the end of the Pen (as shown in Figure 2) before you load a new Syringe Cartridge. If it is sticking out, you will lose that dose.

How to load the IMITREX STATdose Pen

Do not load the Pen until you are ready to give yourself an injection. Do not touch the Blue Button on top of the Pen (see Figure 1) while you are loading the Pen.

Figure 1
Figure 2

1. Open the lid of the Carrying Case.

The tamper-evident seals over the 2 Syringe Cartridges are labeled “A” and “B” (see Figure 1 inset). Always use the Syringe Cartridge marked “A” before the one marked “B” to help you keep track of your doses. Do not use if either seal is broken or missing when you first open the Carrying Case.

2. Tear off one of the tamper-evident seals (see Figure 1). Throw away the seal. Open the lid over the Syringe Cartridge.

3. Hold the Pen by the ridges at the top. Take it out of the Carrying Case (see Figure 2).

Check to make sure the white Priming Rod is not sticking out from the lower end of the Pen (see Figure 2 inset). If it is sticking out, put the Pen back into the Carrying Case and press down firmly until you feel it click. Then take the Pen out of the Carrying Case.

4. Put the Pen in the Cartridge Pack. Turn it to the right (clockwise) until it will not turn any more (about half a turn) (see Figure 3).

Figure 3
Figure 4

5. Hold the loaded Pen by the ridges and pull it straight out (see Figure 4). You may need to pull hard on the Pen, but this is normal. Do not press the Blue Button yet.

The Pen is now ready to use. Do not put the loaded Pen back into the Carrying Case because that will damage the needle.

How to use the IMITREX STATdose Pen to take your medicine

Before injecting your medicine, choose an area with a fatty tissue layer (see Figure 5a or Figure 5b). Ask your healthcare provider if you have a question about where to inject. Clean the skin around this area.

Figure 5a

or

Figure 5b
Figure 6

1. Without pushing the Blue Button, press the loaded Pen firmly against the skin so that the grey barrel slides down toward the blue section that holds the Syringe Cartridge (see Figure 4). (This releases the Safety Catch that keeps the Pen from firing by mistake until you are ready.)

2. Push the Blue Button. Hold the Pen still for at least 5 seconds. If the Pen is taken away from the skin too soon, not all the medicine will come out.

3. After 5 seconds, carefully take the Pen away from your skin. The needle will be showing (see Figure 6). Do not touch the needle.

How to unload the IMITREX STATdose Pen after taking your medicine

Right after you take a dose with the Pen, you need to return the used Syringe Cartridge to the Cartridge Pack.

Figure 7
Figure 8
Figure 9

1. Push the Pen down into the empty side of the Cartridge Pack as far as it will go (see Figure 7).

2. Turn the Pen to the left (counterclockwise) about half a turn until it is released from the Syringe Cartridge (see Figure 8).

3. Pull the empty Pen out of the Cartridge Pack (see Figure 9).

Because the Pen has now been used, the white Priming Rod will stick out from the lower end of the Pen.

4. Close the Cartridge Pack lid over the used Syringe Cartridge. When the used Syringe Cartridges are inserted correctly, the Cartridge Pack is a disposable, protective case to help you avoid needle sticks and use the syringes correctly.

5. Put the Pen back into the Carrying Case and press it down firmly until you feel it click. Close the Carrying Case lid. This gets the Pen ready for the next use.

If the lid will not close, push the Pen down until you feel it click. Then close the lid.

How to take out a used Cartridge Pack

After both Syringe Cartridges have been used, take the Cartridge Pack out of the Carrying Case and throw it away. Never reuse a Syringe Cartridge.

Figure 10
Figure 11

1. Open the Carrying Case lid.

2. Hold the Carrying Case with one hand and press the 2 buttons on either side of the Carrying Case (see Figure 10).

3. Gently pull out the Cartridge Pack with the other hand (see Figure 11).

(continued on other side)

How to insert a new Cartridge Pack

Figure 12
Figure 13
Figure 14

1. Take the new Cartridge Pack out of its box. Do not take off the tamper-evident seals (see Figure 12).

2. Put the Cartridge Pack in the Carrying Case. Slide it down smoothly (see Figure 13).

3. The Cartridge Pack will click into place when the 2 buttons show through the holes in the Carrying Case (see Figure 14). Close the lid.

February 2008

IMJ:2PIL

Information for the Patient

IMITREX® (sumatriptan succinate) Injection

Read this leaflet carefully before you start to take IMITREX Injection. Keep the leaflet for reference because it gives you a summary of important information about IMITREX Injection.

Read the leaflet that comes with each refill of your prescription because there may be new information.

This leaflet does not have all the information about IMITREX Injection. Ask your healthcare provider for more information or advice.

What is IMITREX Injection?

IMITREX Injection is a kind of medicine called a triptan. You should take it only if you have a prescription.

IMITREX Injection is used to relieve your migraine or cluster headache. It is not used to prevent attacks or reduce the number of attacks you have. Use IMITREX Injection only to treat an actual migraine or cluster headache attack.

The decision to use IMITREX Injection is one that you and your healthcare provider should make together, based on your personal needs and health.

Talk with your healthcare provider before taking IMITREX Injection

1. Risk factors for heart disease to tell your healthcare provider:
  Tell your healthcare provider if you have risk factors for heart disease such as:
  - high blood pressure
  - high cholesterol
  - being overweight
  - diabetes
  - smoking
  - strong family history of heart disease
  - you are postmenopausal
  - you are a male over 40 years of age
    If you do have risk factors for heart disease, your healthcare provider should check you for heart disease to see if IMITREX is right for you.
    Although most of the people who have taken IMITREX have not had any serious side effects, some have had serious heart problems. Deaths have been reported, but these were rare considering the extensive worldwide use of IMITREX. Usually, serious problems happened in people with known heart disease. It was not clear whether IMITREX had anything to do with these deaths.
2. Important questions to ask yourself before you take IMITREX Injection:
  If the answer to any of the following questions is YES or if you do not know the answer, then please talk with your healthcare provider before you take IMITREX Injection.
  - Are you pregnant? Do you think you might be pregnant? Are you trying to become pregnant? Are you not using adequate contraception? Are you breastfeeding?
  - Do you have any chest pain, heart disease, shortness of breath, or irregular heartbeats? Have you had a heart attack?
  - Do you have risk factors for heart disease (see list above)?
  - Have you had a stroke, a mini-stroke (also called a transient ischemic attack or TIA), or Raynaud syndrome?
  - Do you have high blood pressure?
  - Have you ever had to stop taking this or any other medicine because of an allergy or other problems?
  - Are you taking any other migraine medicines, including other triptans? Are you taking any medicines containing ergotamine, dihydroergotamine, or methysergide?
  - Are you taking any medicine for depression or other health problems such as a monoamine oxidase inhibitor, selective serotonin reuptake inhibitor (SSRI), or serotonin norepinephrine reuptake inhibitor (SNRI)? Common SSRIs are citalopram HBr (CELEXA®), escitalopram oxalate (LEXAPRO®), paroxetine (PAXIL®), fluoxetine (PROZAC®/SARAFEM®), olanzapine/fluoxetine (SYMBYAX®), sertraline (ZOLOFT®), and fluvoxamine. Common SNRIs are duloxetine (CYMBALTA®) and venlafaxine (EFFEXOR®).
  - Have you had, or do you have, any disease of the liver or kidney?
  - Have you had, or do you have, epilepsy or seizures?
  - Is this headache different from your usual migraine attacks?
    Remember, if you answered YES to any of the above questions, then talk with your healthcare provider about it.

Important points about IMITREX Injection

1. The use of IMITREX Injection during pregnancy:
  Do not take IMITREX Injection if you are pregnant, think you might be pregnant, are trying to become pregnant, or are not using adequate contraception unless you have talked with your healthcare provider about this.
2. How to take IMITREX Injection:
  For adults, the usual dose is a single injection given just below the skin. You should give an injection as soon as the symptoms of your migraine start, but it may be given at any time during an attack. You may give a second injection if your migraine symptoms come back.
  If your symptoms do not get better after the first injection, do not give a second injection for the same attack without first talking with your healthcare provider. Do not give more than two 6-mg doses in any 24-hour period. Allow at least 1 hour between each dose.
3. Caution for activities requiring alertness:
  You may feel drowsy or dizzy because of your migraine or treatment with IMITREX Injection. Use caution for activities requiring alertness (like driving or using machines).
4. What to do if you take an overdose:
  If you have taken more medicine than has been prescribed for you, contact either your healthcare provider, hospital emergency department, or nearest poison control center right away.
5. How to store your medicine:
  Keep your medicine in a safe place where children cannot reach it. It may be harmful to children.
  Store your medicine away from heat and light. Keep your medicine in the Carrying Case that comes with it. Do not store at temperatures above 86°F (30°C).
  The expiration date of your medicine is printed on the back of the Cartridge Pack. If your medicine has expired, throw it away. Do not throw away your IMITREX STATdose Pen®.
  If your healthcare provider decides to stop your treatment, do not keep any leftover medicine unless your healthcare provider tells you to.

Some possible side effects of IMITREX Injection

- Some patients feel pain or tightness in the chest or throat when using IMITREX Injection. If this happens to you, tell your healthcare provider before taking any more IMITREX Injection. If the chest pain, tightness, or pressure is severe or does not go away, call your healthcare provider right away.
- Call your healthcare provider right away if you have sudden and/or severe abdominal pain after you take IMITREX Injection.
- Some people may have a reaction called serotonin syndrome when they take certain kinds of medicines for depression called SSRIs or SNRIs while they are taking IMITREX Injection. Symptoms may include confusion, hallucinations, fast heartbeat, feeling faint, fever, sweating, muscle spasm, difficulty walking, and/or diarrhea. Call your healthcare provider right away if you have any of these symptoms after taking IMITREX Injection.
- Shortness of breath; wheeziness; heart throbbing; swelling of eyelids, face, or lips; or a skin rash, skin lumps, or hives happens rarely. If it happens to you, then tell your healthcare provider right away. Do not take any more IMITREX Injection unless your healthcare provider tells you to.
- Some people may feel tingling, heat, flushing (redness of face lasting a short time), heaviness, or pressure after taking IMITREX Injection. A few people may feel drowsy, dizzy, tired, or sick. If you have any of these symptoms, tell your healthcare provider at your next visit.
- You may have pain or redness at the site of injection, but this usually lasts less than an hour.
- If you feel unwell in any other way or have any symptoms that you do not understand, you should contact your healthcare provider right away.

IMITREX and PAXIL are registered trademarks of GlaxoSmithKline. The other brands listed are trademarks of their respective owners and are not trademarks of GlaxoSmithKline. The makers of these brands are not affiliated with and do not endorse GlaxoSmithKline or its products.

GlaxoSmithKline

Research Triangle Park, NC 27709

©2010, GlaxoSmithKline. All rights reserved.

February 2010

IMJ:2PPI

Principal Display Panel

NDC 54868-3180-0

IMITREX

STATdose SYSTEM®

6 mg

This carton contains:

- Imitrex®

(sumatriptan succinate)

Injection

2 prefilled 0.5-mL syringe cartridges, each containing 6 mg of sumatriptan for subcutaneous injection only

- 1 Imitrex STATdose Pen®
- 1 Carrying Case
- Instructions for Use/Information for the Patient
- Prescribing Information

Rx only